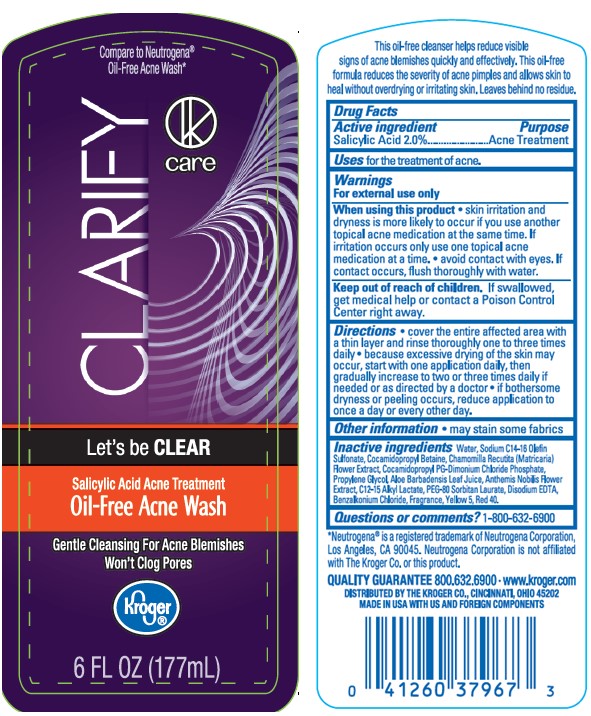 DRUG LABEL: KROGER CLARIFY CARE ACNE WASH
NDC: 30142-945 | Form: LIQUID
Manufacturer: THE KROGER COMPANY
Category: otc | Type: HUMAN OTC DRUG LABEL
Date: 20241015

ACTIVE INGREDIENTS: SALICYLIC ACID 20 mg/1 mL
INACTIVE INGREDIENTS: EDETATE DISODIUM; SODIUM C14-16 OLEFIN SULFONATE; COCAMIDOPROPYL BETAINE; COCAMIDOPROPYL PG-DIMONIUM CHLORIDE PHOSPHATE; PEG-80 SORBITAN LAURATE; C12-15 ALKYL LACTATE; WATER; PROPYLENE GLYCOL; CHAMAEMELUM NOBILE FLOWER; ALOE VERA LEAF; CHAMOMILE; FD&C YELLOW NO. 5; FD&C RED NO. 40; BENZALKONIUM CHLORIDE; ALCOHOL

KROGER CLARIFY CARE OIL-FREE ACNE WASH

Active Ingredients

Salicylic Acid 2.0%

Purpose

Acne Treatment

Uses

for the treatment of acne.

Warnings

For external use only

When using this product

• skin irritation and dryness is more likely to occur if you use another topical acne medication at the same time. If irritation occurs only use one topical acne medication at a time. • avoid contact with eyes. If contact occurs, flush thoroughly with water.

Keep out of reach of children.

If swallowed, get medical help or contact a Poison Control Center immediately.

Directions

- cover the entire affected area with a thin layer and rinse thoroughly one to three times daily
- because excessive drying of the skin may occur, start with one application daily, then gradually increase to two or three times daily if needed or as directed by a doctor
- if bothersome dryness or peeling occurs, reduce application to once a day or every other day

Other information

- may stain some fabrics

Inactive Ingredients

water, sodium C14-16 olefin sulfonate, cocamidopropyl betaine, chamomilla recutita (matricaria) flower extract, cocamidopropyl PG-dimonium chloride phosphate, propylene glycol, aloe barbadensis leaf juice, anthemis nobilis flower extract, C12-15 alkyl lactate, PEG-80 sorbitan laurate, disodium EDTA, benzalkonium chloride, fragrance, yellow 5, red 40.